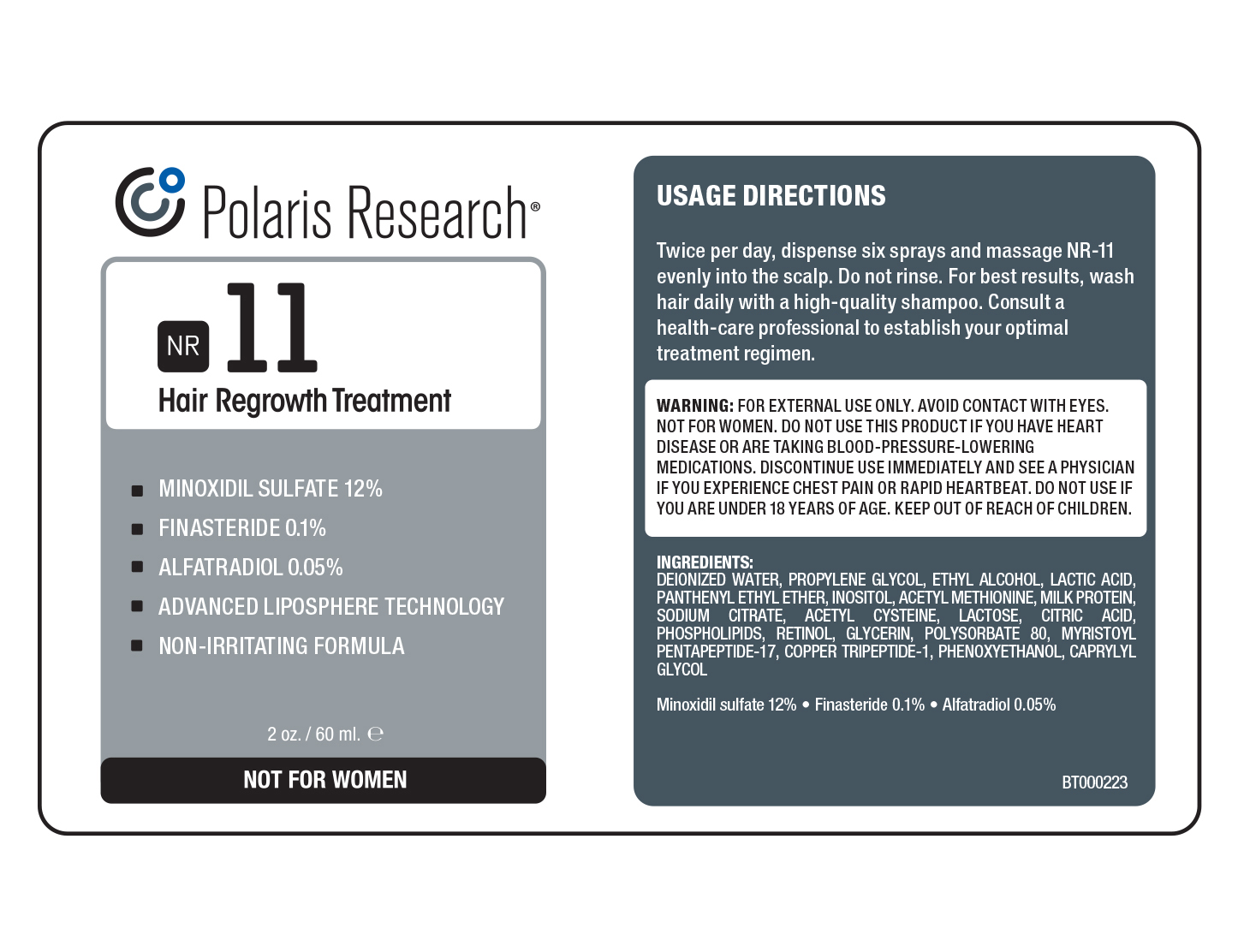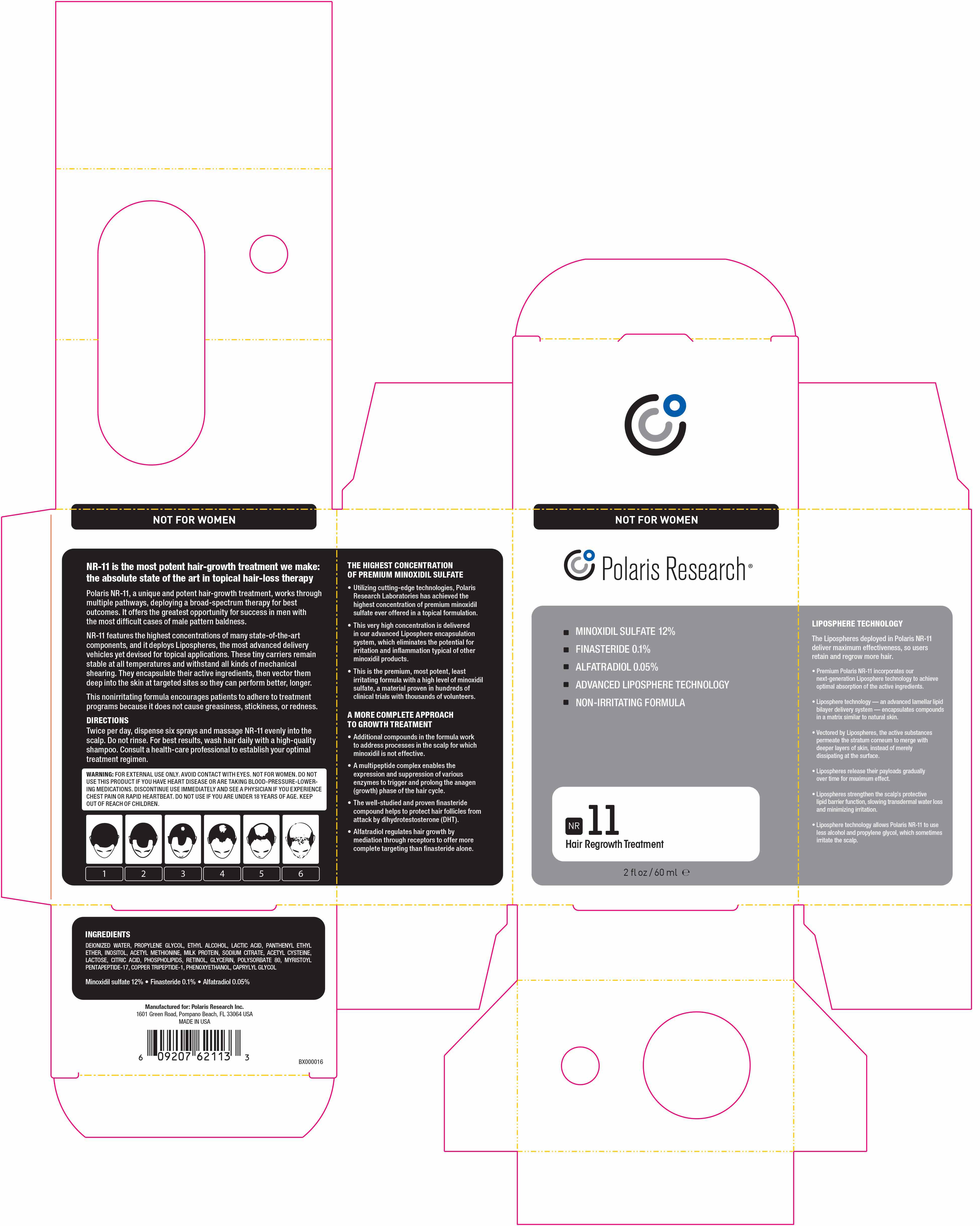 DRUG LABEL: NR-11
NDC: 69188-163 | Form: LIQUID
Manufacturer: DS Healthcare Group Inc.
Category: otc | Type: HUMAN OTC DRUG LABEL
Date: 20170621

ACTIVE INGREDIENTS: ALFATRADIOL 0.05 g/100 g; MINOXIDIL SULFATE ESTER 12 g/100 g; FINASTERIDE 0.01 g/100 g
INACTIVE INGREDIENTS: WATER; PROPYLENE GLYCOL; CASEIN; LACTOSE; CITRIC ACID MONOHYDRATE; LECITHIN, SOYBEAN; INOSITOL; ACETYLCYSTEINE; SODIUM CITRATE; GLYCERIN; POLYSORBATE 80; MYRISTOYL PENTAPEPTIDE-4; PREZATIDE COPPER; PHENOXYETHANOL; CAPRYLYL GLYCOL; ALCOHOL; LACTIC ACID; PANTHENYL ETHYL ETHER; N-ACETYLMETHIONINE; RETINOL

DOSAGE AND ADMINISTRATION

Twice per day, dispense six sprays and massage NR-11 evenly into the
scalp. Do not rinse. For best results, wash hair daily with a high-quality
shampoo. Consult a health-care professional to establish your optimal
treatment regimen.

WARNINGS

FOR EXTERNAL USE ONLY. AVOID CONTACT WITH EYES. NOT FOR WOMEN. DO NOT
USE THIS PRODUCT IF YOU HAVE HEART DISEASE OR ARE TAKING BLOOD-PRESSURE-LOWERING
MEDICATIONS. DISCONTINUE USE IMMEDIATELY AND SEE A PHYSICIAN IF YOU EXPERIENCE
CHEST PAIN OR RAPID HEARTBEAT. DO NOT USE IF YOU ARE UNDER 18 YEARS OF AGE. KEEP
OUT OF REACH OF CHILDREN.

INACTIVE INGREDIENT

DEIONIZED WATER, PROPYLENE GLYCOL, ETHYL ALCOHOL, LACTIC ACID, PANTHENYL ETHYL
ETHER, INOSITOL, ACETYL METHIONINE, MILK PROTEIN, SODIUM CITRATE, ACETYL CYSTEINE,
LACTOSE, CITRIC ACID, PHOSPHOLIPIDS, RETINOL, GLYCERIN, POLYSORBATE 80, MYRISTOYL
PENTAPEPTIDE-17, COPPER TRIPEPTIDE-1, PHENOXYETHANOL, CAPRYLYL GLYCOL

INDICATIONS AND USAGE

Indicated for male pattern balness; for hair-regrowth

PURPOSE

for hair-regrowth

DO NOT USE IF YOU ARE UNDER 18 YEARS OF AGE. KEEP
OUT OF REACH OF CHILDREN.

ACTIVE INGREDIENT

Minoxidil sulfate ............12%

Finasteride..................... 0.1%

Alfatradiol....................... 0.05%